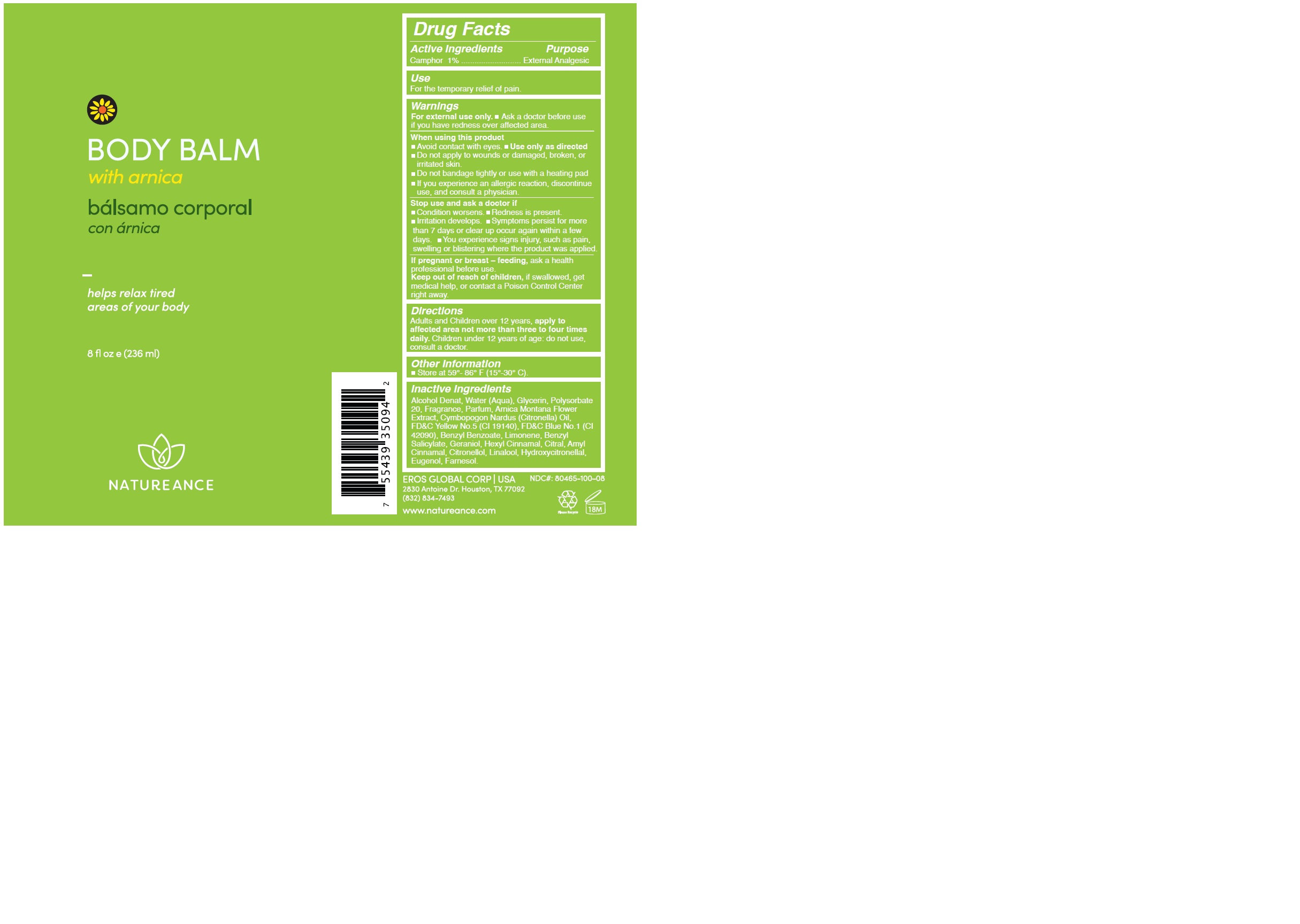 DRUG LABEL: NATUREANCE BODY BALM
NDC: 80465-100 | Form: LIQUID
Manufacturer: EROS GLOBAL CORP
Category: otc | Type: HUMAN OTC DRUG LABEL
Date: 20230919

ACTIVE INGREDIENTS: CAMPHOR (SYNTHETIC) 0.9 g/100 mL
INACTIVE INGREDIENTS: .ALPHA.-HEXYLCINNAMALDEHYDE; LINALOOL, (+/-)-; HYDROXYCITRONELLAL; FARNESOL; .ALPHA.-AMYLCINNAMALDEHYDE; BENZYL SALICYLATE; .BETA.-CITRONELLOL, (R)-; WATER; ALCOHOL; GLYCERIN; POLYSORBATE 20; ARNICA MONTANA FLOWER; LIMONENE, (+/-)-; FD&C BLUE NO. 1; CITRONELLA OIL; FD&C YELLOW NO. 5; BENZYL BENZOATE; GERANIOL; CITRAL; EUGENOL

80465-100-08

ACTIVE INGREDIENT

Camphor 1%

PURPOSE

External Analgesic

USE

For the temporary relief of pain.

WARNINGS

For external use only. · Ask a doctor before use if you have redness over affected area.

WHEN USING

Avoid contact with eyes.
Use only as directed.
Do not apply to wounds or damaged, broken, or irritated skin.
Do not bandage tightly or use with a heating pad

If you experience an allergic reaction, discontinue use, and consult a physician.

STOP USE

Condition worsens.
Redness is present.
Irritation develops.
Symptoms persist for more than 7 days or clear up occur again within a few days.

You experience signs injury, such as pain, swelling or blistering where the product was applied.

If pregnant or breast – feeding

Ask a health professional before use.

KEEP OUT OF REACH OF CHILDREN

If swallowed, get medical help, or contact a Poison Control Center right away.

DIRECTIONS

Adults and Children over 12 years

Apply to affected area not more than three to four times daily.

Children under 12 years of age: do not use, consult a doctor.

OTHER SAFETY INFORMATION

Store tightly closed in a dry place at controlled room temperature between 59°-86° F (15°-30° C).

INACTIVE INGREDIENT

Alcohol Denat, Water (Aqua), Glycerin, Polysorbate 20, Fragrance, Parfum, Arnica Montana Flower Extract, Cymbopogon Nardus (Citronella) Oil, FD&C Yellow No.5 (CI 19140), FD&C Blue No.1 (CI 42090), Benzyl Benzoate, Limonene, Benzyl Salicylate, Geraniol, Hexyl Cinnamal, Citral, Amyl Cinnamal, Citronellol, Linalool, Hydroxycitronellal, Eugenol, Farnesol.